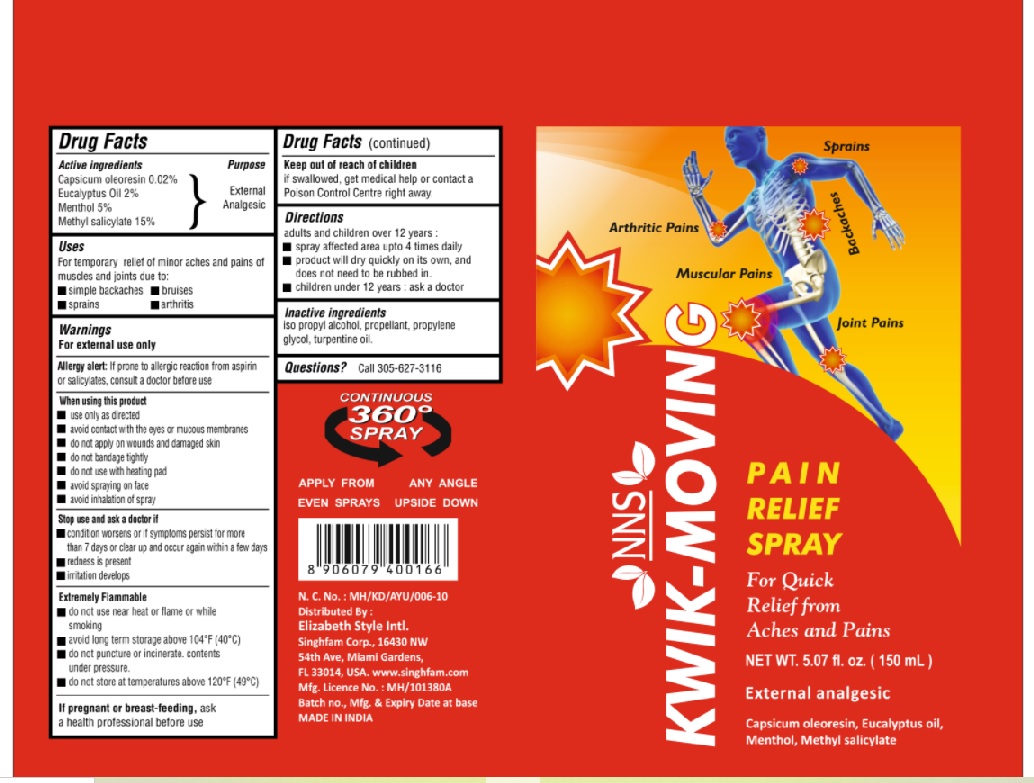 DRUG LABEL: KWIK-MOVING
NDC: 73640-020 | Form: SPRAY
Manufacturer: N. N. IMPEX
Category: otc | Type: HUMAN OTC DRUG LABEL
Date: 20210301

ACTIVE INGREDIENTS: EUCALYPTUS OIL 2 g/100 mL; MENTHOL 5 g/100 mL; METHYL SALICYLATE 15 g/100 mL; CAPSICUM OLEORESIN 0.02 g/100 mL
INACTIVE INGREDIENTS: ISOPROPYL ALCOHOL; LIQUEFIED PETROLEUM GAS; PROPYLENE GLYCOL; TURPENTINE OIL

Active ingredients

Capsicum oleoresin 0.02% ,Eucalyptus Oil 2% ,Menthol 5% ,Methyl salicylate 15%

Purpose

External Analgesic

Warning

For external use only.

Allergy alert:If prone to allergic reaction from aspirin or salicylates, consult a doctor before use.

Stop use and ask a doctor if condition worsens or if symptoms persist for more than 7 days or clear up and occurs again within a few days. Redness is present. Irritation develops.

When using this product

Use only as directed. Avoid contact with the eyes or mucous membranes. Do not apply on wounds and damaged skin. Do not bandage tightly.

Do not use with heating pad. Avoid spraying on face. Avoid inhalation of spray.

If pregnant or breast-feeding, ask a health professional before use.

Extremely Flammable

do not use near heat or flame or while smoking. Avoid long term storage above 104 °F (40 °C)do not puncture or incinerate. Contents
under pressure. Do not store at temperatures above 120 °F (49 °C).

Uses

For temporary relief of minor aches and pains of muscles and joints due to: simple backaches, bruises, sprains, arthritis

Direction

Adults and children over 12 years : spray affected area up to 4 times daily. product will dry quickly on its own, and
does not need to be rubbed in. Children under 12 years : ask a doctor

Keep out of reach of children

If swallowed, get medical help or contact a Poison Control Center right away.

Inactive Ingredient

Isopropyl alcohol, propellant, propylene glycol, turpentine oil.